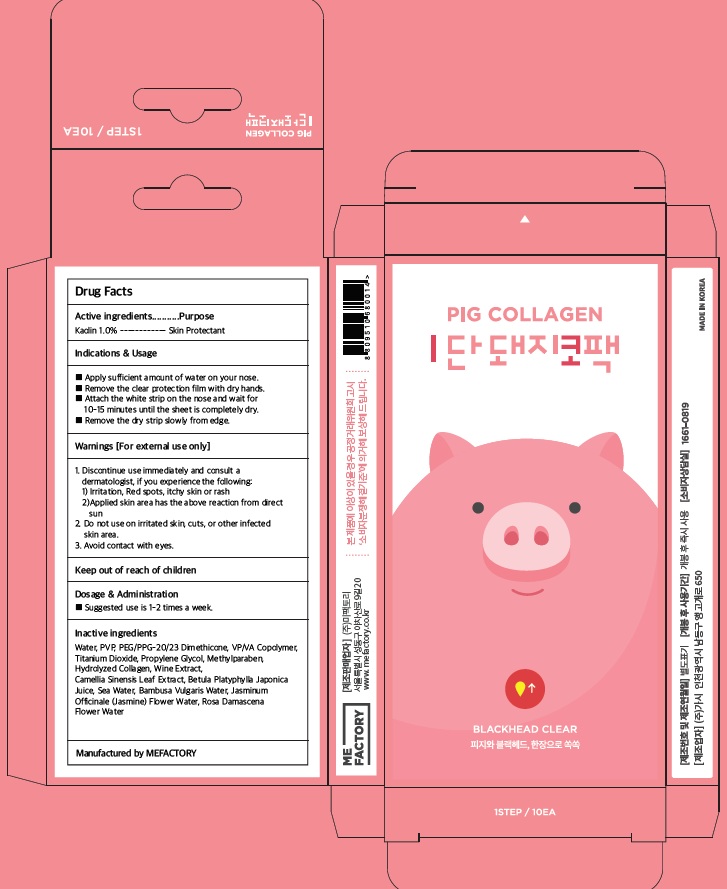 DRUG LABEL: MEFACTORY PIG COLLAGEN 1STEP PIGGY NOSE PACK
NDC: 70908-040 | Form: PATCH
Manufacturer: MeFactory Co., Ltd.
Category: otc | Type: HUMAN OTC DRUG LABEL
Date: 20170103

ACTIVE INGREDIENTS: Kaolin 0.002 g/0.2 g
INACTIVE INGREDIENTS: Water; Titanium Dioxide

ACTIVE INGREDIENT

Active Ingredient: Kaolin 1.0%

INACTIVE INGREDIENT

Inactive Ingredients: Water, PVP, PEG/PPG-20/23 Dimethicone, VP/VA Copolymer, Titanium Dioxide, Propylene Glycol, Methylparaben, Hydrolyzed Collagen, Wine Extract, Camellia Sinensis Leaf Extract, Betula Platyphylla Japonica Juice, Sea Water, Bambusa Vulgaris Water, Jasminum Officinale (Jasmine) Flower Water, Rosa Damascena Flower Water

PURPOSE

Purpose: Skin Protectant

WARNINGS

Warnings: 1. Discontinue use immediately and consult a dermatologist, if you experience the following: 1) Irritation, Red spots, itchy skin or rash 2) Applied skin area has the above reaction from direct sun 2. Do not use on irritated skin, cuts, or other infected skin area. 3. Avoid contact with eyes.

KEEP OUT OF REACH OF CHILDREN

INDICATIONS & USAGE

Indications and usage: Apply sufficient amount of water on your nose. Remove the clear protection film with dry hands. Attach the white strip on the nose and wait for 10-15 minutes until the sheet is completely dry. Remove the dry strip slowly from edge.

DOSAGE & ADMINISTRATION

Dosage and administration: Suggested use is 1-2 times a week